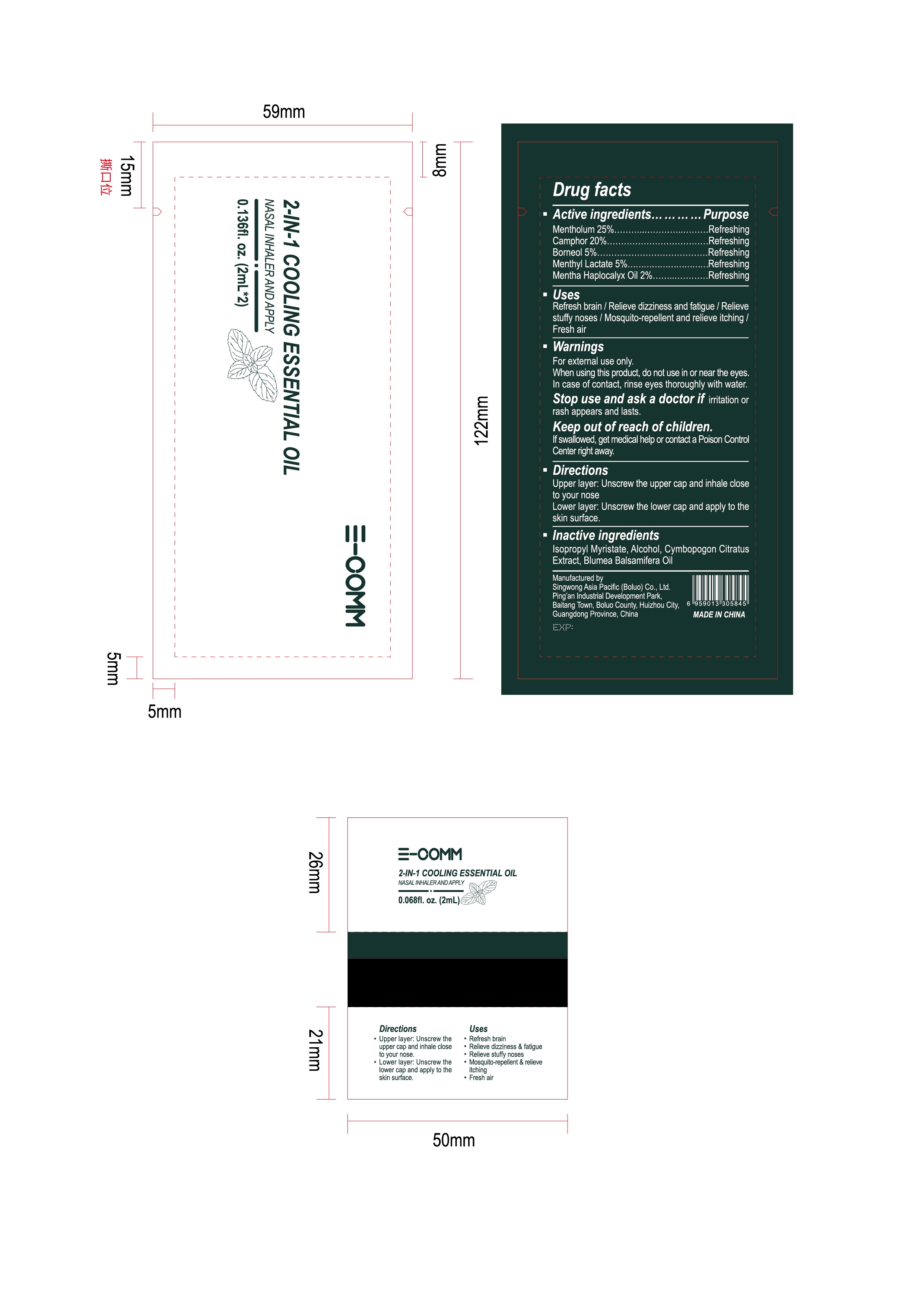 DRUG LABEL: Cooling Essential Oil
NDC: 82421-001 | Form: OIL
Manufacturer: Shenzhen E-commerce Trading Co., Ltd
Category: otc | Type: HUMAN OTC DRUG LABEL
Date: 20211124

ACTIVE INGREDIENTS: MENTHYL LACTATE, (-)- 5 mg/100 mL; MENTHA CANADENSIS TOP 2 mg/100 mL; MENTHOL 25 mg/100 mL; CAMPHOR OIL 20 mg/100 mL; BORNEOL 5 mg/100 mL
INACTIVE INGREDIENTS: ALCOHOL

2-IN-1 COOLING ESSENTIAL OIL

ACTIVE INGREDIENT

Mentholum 25%, Camphor 20%, Borneol 5%, Menthyl Lactate 5%, Mentha Haplocalyx Oil 2%

PURPOSE

Refresh brain / Relieve dizziness and fatigue / Relieve stuff noses / Mosquito-repellent and relieve itching / Fresh air

WARNINGS

For external use only.

When using this product, do not use in or near the eyes. In case of contact, rinse eyes thoroughly with water.

Stop use and ask a doctor

If irritation or rash appears and lasts, stop use the product.In case of accidental ingestion, contact a doctor

KEEP OUT OF REACH OF CHILDREN

If swallowed, get medical help or contact a Poison Control Cneter right away.

INSTRUCTIONS FOR USE

Upper layer: Unscrew the upper cap and inhale close to your nose.

Lower layer: Unscrew the lower cap and apply to the skin surface.

INACTIVE INGREDIENT

Isopropyl Myristate, Alcohol, Cymbopogon Citratus Extract, Blumea Balsamifera Oil.

DOSAGE AND ADMINISTRATION

Max 4 times on day

INDICATIONS AND USAGE

Unscrew the upper cap and inhale close to your nose.

Unscrew the lower cap and apply to the skin surface.